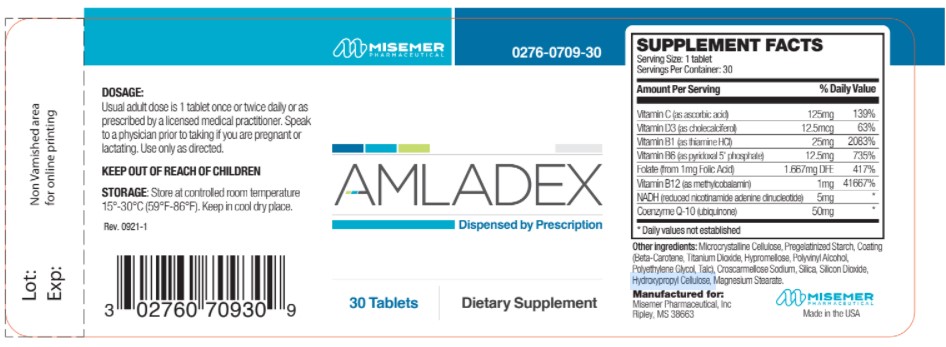 DRUG LABEL: Amladex
NDC: 0276-0709 | Form: TABLET
Manufacturer: Misemer Pharmaceuticals, Inc.
Category: other | Type: DIETARY SUPPLEMENT
Date: 20211116

ACTIVE INGREDIENTS: ASCORBIC ACID 125 mg/1 1; CHOLECALCIFEROL 12.5 ug/1 1; THIAMINE HYDROCHLORIDE 25 mg/1 1; PYRIDOXAL PHOSPHATE ANHYDROUS 12.5 mg/1 1; FOLIC ACID 1.667 mg/1 1; METHYLCOBALAMIN 1 mg/1 1; NADH 5 mg/1 1; COENZYME Q10, (2Z)- 50 mg/1 1
INACTIVE INGREDIENTS: CELLULOSE, MICROCRYSTALLINE; MAGNESIUM STEARATE; SILICON DIOXIDE; CROSCARMELLOSE SODIUM; HYDROXYPROPYL CELLULOSE, UNSPECIFIED

AmladexTablets

HEALTH CLAIM:

Amladex Tablets Dietary Supplement

Dispensed by Prescription†

Supplement Facts
Serving Size: 1 Tablet
Servings per Bottle: 30
Amount Per Serving: | % Daily Value
Vitamin C (as ascorbic acid) | 125 mg | 208%
Vitamin D3 (as cholecalciferol) | 500 IU | 125%
Vitamin B1 (as Thiamin HCl) | 25 mg | 1,667%
Vitamin B6 (as pyridoxal phosphate anhydrous) | 12.5 mg | 625%
Folic Acid | 1.667 mg | 250%
Vitamin B12 (as methylcobalamin) | 1 mg | 16,667%
NADH (reduced nicotinamide-adenine dinucleotide) | 5 mg | *
CoEnzyme Q-10 (ubiquinone) | 50 mg | *
*Daily Values (DV) not established.

OTHER INGREDIENTS: Microcrystalline Cellulose, Croscarmellose Sodium, Silicon Dioxide, Magnesium Stearate..

DESCRIPTION:

Amladex is an orally administered prescription vitamin formulation for the clinical dietary management of suboptimal nutritional status in patients where advanced folate supplementation is required and nutritional supplementation in physiologically stressful conditions for maintenance of good health is needed.

Amladex should be administered under the supervision of a licensed medical practitioner.

WARNING AND PRECAUTIONS

This product is contraindicated in patients with a known hypersensitivity to any of the ingredients.

Amladex should only be used under the direction and supervision of a licensed medical practitioner. Use with caution in patients that may have a medical condition, are pregnant, lactating, trying to conceive, under the age of 18, or taking medications.

DOSAGE & ADMINISTRATION

Usual adult dose is 1 tablet once or twice daily or as prescribed by a licensed medical practitioner.

INDICATIONS AND USAGE
Amladex is an orally administered prescription vitamin formulation for the clinical dietary management of suboptimal nutritional status in patients where advanced folate supplementation is required and nutritional supplementation in physiologically stressful conditions for maintenance of good health is needed.

HOW SUPPLIED HEALTH CLAIM:

Amladex is supplied as a clear coated oblong tablet dispensed in HDPE plastic bottles of 30ct.

Dispensed by Prescription†

Reserved for Professional Recommendation

All prescriptions using this product shall be pursuant to state statutes as applicable. This is not an Orange Book product. This product may be administered only under a physician’s supervision. There are no implied or explicit claims on therapeutic equivalence.

† This product is a prescription-folate with or without other dietary ingredients that – due to increased folate levels increased risk associated with masking of B12 deficiency (pernicious anemia) requires administration under the care of a licensed medical practitioner (61 FR 8760).1-3 The most appropriate way to ensure pedigree reporting consistent with these regulatory guidelines and safety monitoring is to dispense this product only by prescription (Rx). This is not an Orange Book product. This product may be administered only under a physician’s supervision and all prescriptions using this product shall be pursuant to state statutes as applicable. The ingredients, indication or claims of this product are not to be construed to be drug claims.

1. Federal Register Notice of August 2, 1973 (38 FR 20750)

2. Federal Register Notice of October 17, 1980 (45 FR 69043, 69044)

3. Federal Register Notice of March 5, 1996 (61 FR 8760)

Manufactured for:

Misemer Pharmaceuticals, Inc.

Ripley, MS 38663

Rev. 11/21

STORAGE AND HANDLING:

Store at controlled room temperature 15°-30°C (59°F-86°F). Keep in cool dry place. Call your doctor about side effects. You may report side effects to FDA at 1-800-FDA-1088.

KEEP THIS OUT OF THE REACH OF CHILDREN.